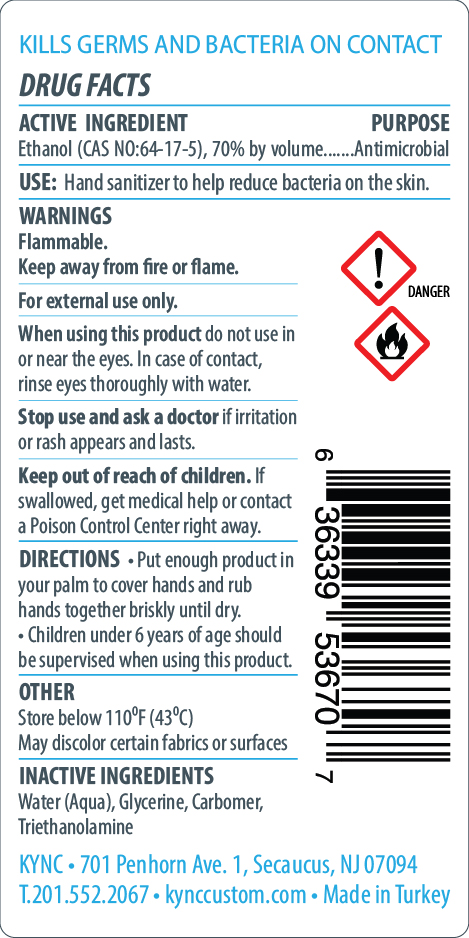 DRUG LABEL: Juniper Clean Hand Sanitizer
NDC: 76557-000 | Form: GEL
Manufacturer: KYNC Design LLC
Category: otc | Type: HUMAN OTC DRUG LABEL
Date: 20260123

ACTIVE INGREDIENTS: ALCOHOL 70 mL/100 mL
INACTIVE INGREDIENTS: TROLAMINE; GLYCERIN; CARBOMER 1342; WATER

Hand Sanitizer

SPL Unclassified Section

Active Ingredient(s)

Ethanol 70% v/v. Purpose: Antimicrobial

Purpose

Antimicrobial, Hand Sanitizer

Use

Hand Sanitizer to help reduce bacteria on the skin.

Warnings

Flammable. Keep away from fire or flame.

For extarnal use only.

Do not use

- in children less than 2 months of age
- on open skin wounds

When using this product do not use in or near the eyes. In case of contact, rinse eyes throughly with water.

Stop use and ask a doctor if irritation or rash appears and lasts.

Keep out of reach of children. If swallowed, get medical help or contact a Poison Control Center right away.

Directions

- Put enough product in your palm to cover hands and rub hands together briskly until dry.
- Children under 6 years of age should be supervised when using this product.

Other information

Store below 110F (43C)

May discolor certain fabrics or surfaces

Inactive ingredients

Water (Aqua), Glycerine, Carbomer, Triethanolamine

Package Label - Principal Display Panel

250 mL NDC: 76557-000-02